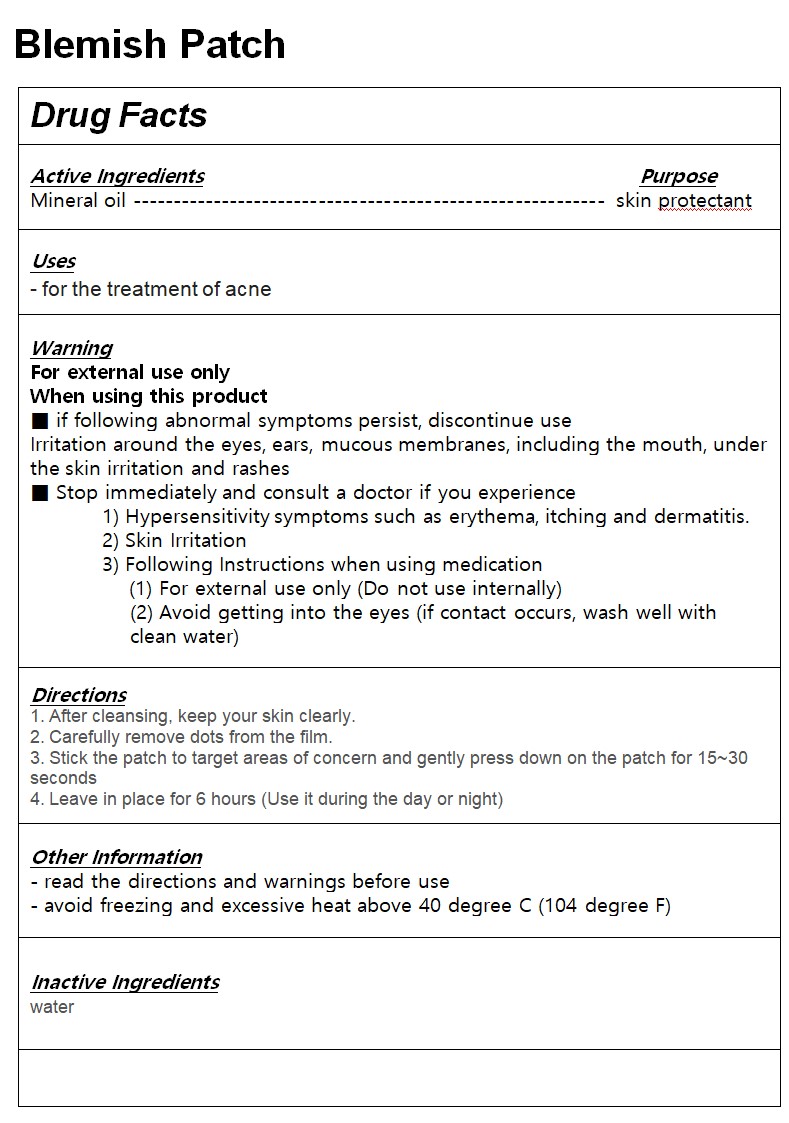 DRUG LABEL: HANHOO BlemishPatch
NDC: 83857-0001 | Form: PATCH
Manufacturer: New Bio Pharmaceutical Co., Ltd.
Category: otc | Type: HUMAN OTC DRUG LABEL
Date: 20231207

ACTIVE INGREDIENTS: MINERAL OIL 4.25 g/100 g
INACTIVE INGREDIENTS: WATER

ACTIVE INGREDIENT

mineral oil

PURPOSE

skin protectant

for the treatment of acne

Keep out of reach of children

INDICATIONS AND USAGE

1. After cleansing, keep your skin clearly.

2. Carefully remove dots from the film.

3. Stick the patch to target areas of concern and gently press down on the patch for 15~30 seconds

4. Leave in place for 6 hours (Use it during the day or night)

WARNINGS

For external use only

When using this product

■ if following abnormal symptoms persist, discontinue use

Irritation around the eyes, ears, mucous membranes, including the mouth, under the skin irritation and rashes

■ Stop immediately and consult a doctor if you experience

1) Hypersensitivity symptoms such as erythema, itching and dermatitis.

2) Skin Irritation

3) Following Instructions when using medication

(1) For external use only (Do not use internally)

(2) Avoid getting into the eyes (if contact occurs, wash well with clean water)

INACTIVE INGREDIENT

water

DOSAGE AND ADMINISTRATION

For topical use only